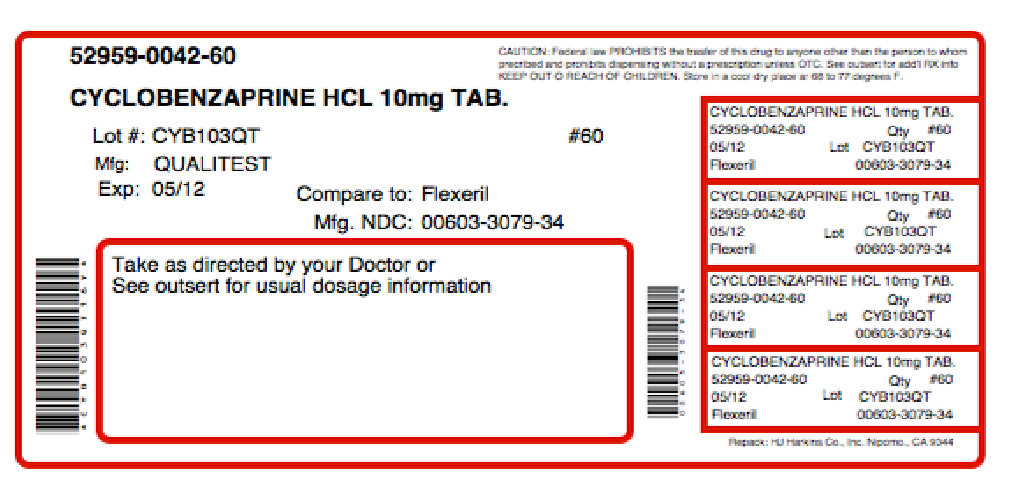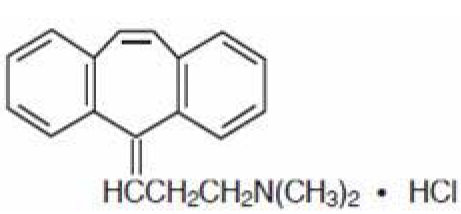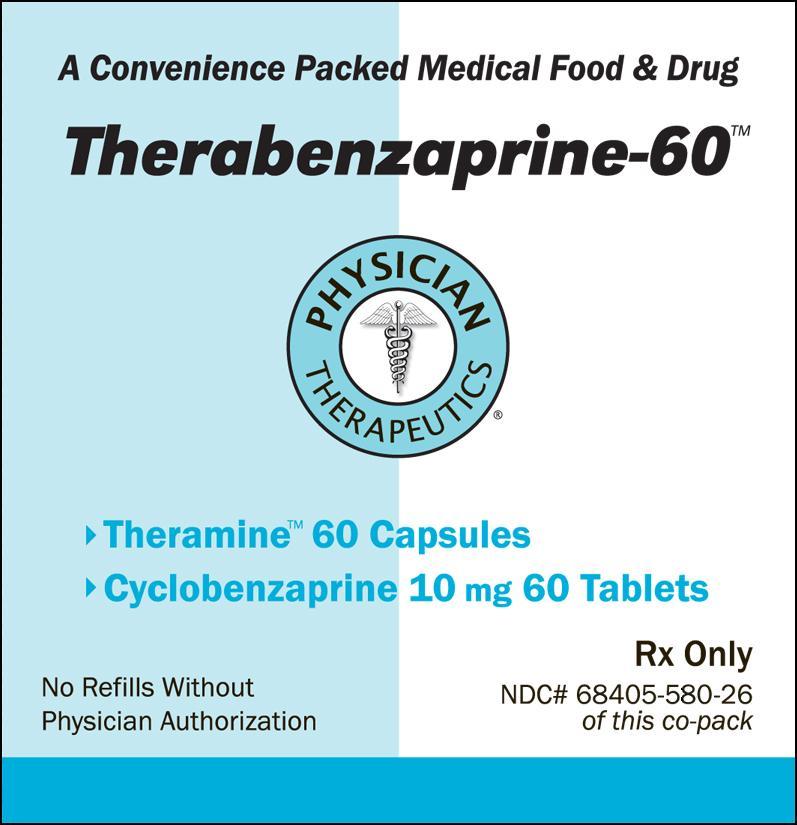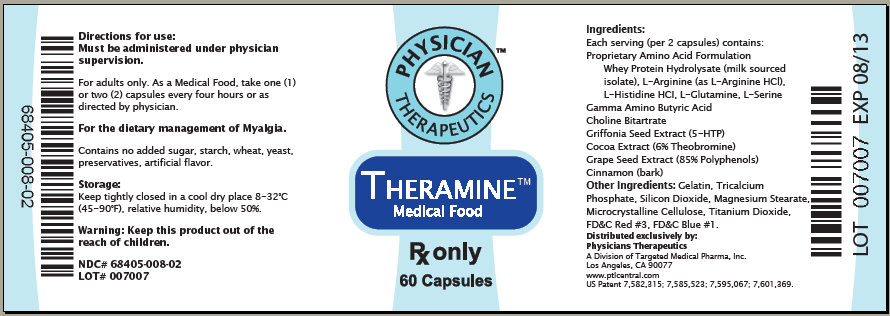 DRUG LABEL: Therabenzaprine-60
NDC: 68405-580 | Form: KIT | Route: ORAL
Manufacturer: Physician Therapeutics LLC
Category: prescription | Type: HUMAN PRESCRIPTION DRUG LABEL
Date: 20110801

ACTIVE INGREDIENTS: CYCLOBENZAPRINE HYDROCHLORIDE 10 mg/1 1; .GAMMA.-AMINOBUTYRIC ACID 100 mg/1 1
INACTIVE INGREDIENTS: CROSCARMELLOSE SODIUM; FD&C YELLOW NO. 6; HYPROMELLOSES; LACTOSE MONOHYDRATE; MAGNESIUM STEARATE; CELLULOSE, MICROCRYSTALLINE; POLYETHYLENE GLYCOL; TITANIUM DIOXIDE; D&C YELLOW NO. 10; POLYSORBATE 80; GELATIN; SILICON DIOXIDE; TRICALCIUM PHOSPHATE; POWDERED CELLULOSE; FD&C BLUE NO. 1; FD&C RED NO. 3; TITANIUM DIOXIDE

Therabenzaprine-60

DESCRIPTION

Cyclobenzaprine hydrochloride is a white, crystalline tricyclic amine salt with the empirical formula C20H21N • HCl and a molecular weight of 311.9. It has a melting point of 217°C, and a pKa of 8.47 at 25°C. It is freely soluble in water and alcohol, sparingly soluble in isopropanol, and insoluble in hydrocarbon solvents. If aqueous solutions are made alkaline, the free base separates.

Cyclobenzaprine HCl is designated chemically as 3-(5H-dibenzo[a,d]cyclohepten-5-ylidene)-N,N-dimethyl-1-propanamine hydrochloride, and has the following structural formula:

Cyclobenzaprine Hydrochloride Tablets, USP are supplied as 5 mg and 10 mg tablets for oral administration.

Each tablet contains the following inactive ingredients: croscarmellose sodium, FD C Yellow #6, hypromellose, lactose monohydrate, magnesium stearate, microcrystalline cellulose, polyethylene glycol, and titanium dioxide; 5 mg tablets also contain FD C Red #40 and 10 mg tablets contain D C Yellow #10 and polysorbate.

CLINICAL PHARMACOLOGY

Cyclobenzaprine HCl relieves skeletal muscle spasm of local origin without interfering with muscle function. It is ineffective in muscle spasm due to central nervous system disease.

Cyclobenzaprine reduced or abolished skeletal muscle hyperactivity in several animal models. Animal studies indicate that cyclobenzaprine does not act at the neuromuscular junction or directly on skeletal muscle. Such studies show that cyclobenzaprine acts primarily within the central nervous system at brain stem as opposed to spinal cord levels, although its action on the latter may contribute to its overall skeletal muscle relaxant activity. Evidence suggests that the net effect of cyclobenzaprine is a reduction of tonic somatic motor activity, influencing both gamma (γ) and alpha (α) motor systems.

Pharmacological studies in animals showed a similarity between the effects of cyclobenzaprine and the structurally related tricyclic antidepressants, including reserpine antagonism, norepinephrine potentiation, potent peripheral and central anticholinergic effects, and sedation. Cyclobenzaprine caused slight to moderate increase in heart rate in animals.

Pharmacokinetics

Estimates of mean oral bioavailability of cyclobenzaprine range from 33% to 55%. Cyclobenzaprine exhibits linear pharmacokinetics over the dose range 2.5 mg to 10 mg, and is subject to enterohepatic circulation. It is highly bound to plasma proteins. Drug accumulates when dosed three times a day, reaching steady state within 3-4 days at plasma concentrations about four-fold higher than after a single dose. At steady state in healthy subjects receiving 10 mg t.i.d. (n=18), peak plasma concentration was 25.9 ng/mL (range, 12.8-46.1 ng/mL), and area under the concentration-time (AUC) curve over an 8-hour dosing interval was 177 ng•hr/mL (range, 80-319 ng•hr/mL).

Cyclobenzaprine is extensively metabolized, and is excreted primarily as glucuronides via the kidney. Cytochromes P-450 3A4, 1A2, and, to a lesser extent, 2D6, mediate N-demethylation, one of the oxidative pathways for cyclobenzaprine. Cyclobenzaprine is eliminated quite slowly, with an effective half-life of 18 hours (range 8-37 hours; n=18); plasma clearance is 0.7 L/min.

The plasma concentration of cyclobenzaprine is generally higher in the elderly and in patients with hepatic impairment (see PRECAUTIONS, Use in the Elderly and PRECAUTIONS, Impaired Hepatic Function).

Elderly

In a pharmacokinetic study in elderly individuals (≥65 yrs old), mean (n=10) steady state cyclobenzaprine AUC values were approximately 1.7-fold (171.0 ng•hr/mL, range 96.1-255.3) higher than those seen in a group of eighteen younger adults (101.4 ng•hr/mL, range 36.1-182.9) from another study. Elderly male subjects had the highest observed mean increase, approximately 2.4-fold (198.3 ng•hr/mL, range 155.6-255.3 versus 83.2 ng•hr/mL, range 41.1-142.5 for younger males) while levels in elderly females were increased to a much lesser extent, approximately 1.2-fold (143.8 ng•hr/mL, range 96.1-196.3 versus 115.9 ng•hr/mL, range 36.1-182.9 for younger females).

In light of these findings, therapy with cyclobenzaprine hydrochloride tablets in the elderly should be initiated with a 5 mg dose and titrated slowly upward.

Hepatic Impairment

In a pharmacokinetic study of sixteen subjects with hepatic impairment (15 mild, 1 moderate per Child-Pugh score), both AUC and Cmax were approximately double the values seen in the healthy control group. Based on the findings, cyclobenzaprine hydrochloride tablets should be used with caution in subjects with mild hepatic impairment starting with the 5 mg dose and titrating slowly upward. Due to the lack of data in subjects with more severe hepatic insufficiency, the use of cyclobenzaprine hydrochloride tablets in subjects with moderate to severe impairment is not recommended.

No significant effect on plasma levels or bioavailability of cyclobenzaprine hydrochloride tablets or aspirin was noted when single or multiple doses of the two drugs were administered concomitantly. Concomitant administration of cyclobenzaprine hydrochloride tablets and naproxen or diflunisal was well tolerated with no reported unexpected adverse effects. However combination therapy of cyclobenzaprine hydrochloride tablets with naproxen was associated with more side effects than therapy with naproxen alone, primarily in the form of drowsiness. No well-controlled studies have been performed to indicate that cyclobenzaprine hydrochloride tablets enhance the clinical effect of aspirin or other analgesics, or whether analgesics enhance the clinical effect of cyclobenzaprine hydrochloride tablets in acute musculoskeletal conditions.

Clinical Studies

Eight double-blind controlled clinical studies were performed in 642 patients comparing cyclobenzaprine hydrochloride 10 mg, diazepam, and placebo. Muscle spasm, local pain and tenderness, limitation of motion, and restriction in activities of daily living were evaluated. In three of these studies there was a significantly greater improvement with cyclobenzaprine than with diazepam, while in the other studies the improvement following both treatments was comparable.

Although the frequency and severity of adverse reactions observed in patients treated with cyclobenzaprine were comparable to those observed in patients treated with diazepam, dry mouth was observed more frequently in patients treated with cyclobenzaprine and dizziness more frequently in those treated with diazepam. The incidence of drowsiness, the most frequent adverse reaction, was similar with both drugs.

The efficacy of cyclobenzaprine hydrochloride tablets 5 mg was demonstrated in two seven-day, double-blind, controlled clinical trials enrolling 1405 patients. One study compared cyclobenzaprine hydrochloride tablets 5 and 10 mg t.i.d. to placebo; and a second study compared cyclobenzaprine hydrochloride tablets 5 and 2.5 mg t.i.d. to placebo. Primary endpoints for both trials were determined by patient-generated data and included global impression of change, medication helpfulness, and relief from starting backache. Each endpoint consisted of a score on a 5-point rating scale (from 0 or worst outcome to 4 or best outcome). Secondary endpoints included a physician's evaluation of the presence and extent of palpable muscle spasm.

Comparisons of cyclobenzaprine hydrochloride tablets 5 mg and placebo groups in both trials established the statistically significant superiority of the 5 mg dose for all three primary endpoints at day 8 and, in the study comparing 5 and 10 mg, at day 3 or 4 as well. A similar effect was observed with cyclobenzaprine hydrochloride tablets 10 mg (all endpoints). Physician-assessed secondary endpoints also showed that cyclobenzaprine hydrochloride tablets 5 mg was associated with a greater reduction in palpable muscle spasm than placebo.

Analysis of the data from controlled studies shows that cyclobenzaprine produces clinical improvement whether or not sedation occurs.

Surveillance Program

A post-marketing surveillance program was carried out in 7607 patients with acute musculoskeletal disorders, and included 297 patients treated with cyclobenzaprine hydrochloride tablets 10 mg for 30 days or longer. The overall effectiveness of cyclobenzaprine was similar to that observed in the double-blind controlled studies; the overall incidence of adverse effects was less (see ADVERSE REACTIONS).

INDICATIONS AND USAGE

Cyclobenzaprine hydrochloride tablets are indicated as an adjunct to rest and physical therapy for relief of muscle spasm associated with acute, painful musculoskeletal conditions.

Improvement is manifested by relief of muscle spasm and its associated signs and symptoms, namely, pain, tenderness, limitation of motion, and restriction in activities of daily living.

Cyclobenzaprine hydrochloride tablets should be used only for short periods (up to two or three weeks) because adequate evidence of effectiveness for more prolonged use is not available and because muscle spasm associated with acute, painful musculoskeletal conditions is generally of short duration and specific therapy for longer periods is seldom warranted.

Cyclobenzaprine hydrochloride tablets have not been found effective in the treatment of spasticity associated with cerebral or spinal cord disease, or in children with cerebral palsy.

CONTRAINDICATIONS

Hypersensitivity to any component of this product.

Concomitant use of monoamine oxidase (MAO) inhibitors or within 14 days after their discontinuation. Hyperpyretic crisis seizures, and deaths have occurred in patients receiving cyclobenzaprine (or structurally similar tricyclic antidepressants) concomitantly with MAO inhibitor drugs.

Acute recovery phase of myocardial infarction, and patients with arrhythmias, heart block or conduction disturbances, or congestive heart failure.

Hyperthyroidism.

WARNINGS

Cyclobenzaprine is closely related to the tricyclic antidepressants, e.g., amitriptyline and imipramine. In short term studies for indications other than muscle spasm associated with acute musculoskeletal conditions, and usually at doses somewhat greater than those recommended for skeletal muscle spasm, some of the more serious central nervous system reactions noted with the tricyclic antidepressants have occurred (see WARNINGS, below, and ADVERSE REACTIONS).

Tricyclic antidepressants have been reported to produce arrhythmias, sinus tachycardia, prolongation of the conduction time leading to myocardial infarction and stroke.

Cyclobenzaprine may enhance the effects of alcohol, barbiturates, and other CNS depressants.

PRECAUTIONS

PRECAUTIONSGeneral

Because of its atropine-like action, cyclobenzaprine hydrochloride should be used with caution in patients with a history of urinary retention, angle-closure glaucoma, increased intraocular pressure, and in patients taking anticholinergic medication.

Impaired Hepatic Function

The plasma concentration of cyclobenzaprine is increased in patients with hepatic impairment (see CLINICAL PHARMACOLOGY, Pharmacokinetics, Hepatic Impairment).

These patients are generally more susceptible to drugs with potentially sedating effects, including cyclobenzaprine. Cyclobenzaprine hydrochloride tablets should be used with caution in subjects with mild hepatic impairment starting with a 5 mg dose and titrating slowly upward. Due to the lack of data in subjects with more severe hepatic insufficiency, the use of cyclobenzaprine hydrochloride tablets in subjects with moderate to severe impairment is not recommended.

Information for Patients

Cyclobenzaprine hydrochloride tablets, especially when used with alcohol or other CNS depressants, may impair mental and/or physical abilities required for performance of hazardous tasks, such as operating machinery or driving a motor vehicle. In the elderly, the frequency and severity of adverse events associated with the use of cyclobenzaprine, with or without concomitant medications, is increased. In elderly patients, cyclobenzaprine hydrochloride tablets should be initiated with a 5 mg dose and titrated slowly upward.

Drug Interactions

Cyclobenzaprine may have life-threatening interactions with MAO inhibitors (see CONTRAINDICATIONS).

Cyclobenzaprine may enhance the effects of alcohol, barbiturates, and other CNS depressants.

Tricyclic antidepressants may block the antihypertensive action of guanethidine and similarly acting compounds.

Tricyclic antidepressants may enhance the seizure risk in patients taking tramadol.

Carcinogenesis, Mutagenesis, Impairment of Fertility

In rats treated with cyclobenzaprine hydrochloride for up to 67 weeks at doses of approximately 5 to 40 times the maximum recommended human dose, pale, sometimes enlarged, livers were noted and there was a dose-related hepatocyte vacuolation with lipidosis. In the higher dose groups this microscopic change was seen after 26 weeks and even earlier in rats which died prior to 26 weeks; at lower doses, the change was not seen until after 26 weeks.

Cyclobenzaprine did not affect the onset, incidence or distribution of neoplasia in an 81-week study in the mouse or in a 105-week study in the rat.

At oral doses of up to 10 times the human dose, cyclobenzaprine did not adversely affect the reproductive performance or fertility of male or female rats. Cyclobenzaprine did not demonstrate mutagenic activity in the male mouse at dose levels of up to 20 times the human dose.

Pregnancy Pregnancy Category B:

Reproduction studies have been performed in rats, mice and rabbits at doses up to 20 times the human dose, and have revealed no evidence of impaired fertility or harm to the fetus due to cyclobenzaprine. There are, however, no adequate and well-controlled studies in pregnant women. Because animal reproduction studies are not always predictive of human response, this drug should be used during pregnancy only if clearly needed.

Nursing Mothers

It is not known whether this drug is excreted in human milk. Because cyclobenzaprine is closely related to the tricyclic antidepressants, some of which are known to be excreted in human milk, caution should be exercised when cyclobenzaprine hydrochloride is administered to a nursing woman.

Pediatric Use

Safety and effectiveness of cyclobenzaprine hydrochloride in pediatric patients below 15 years of age have not been established.

Use in the Elderly

The plasma concentration of cyclobenzaprine is increased in the elderly (see CLINICAL PHARMACOLOGY, Pharmacokinetics, Elderly). The elderly may also be more at risk for CNS adverse events such as hallucinations and confusion, cardiac events resulting in falls or other sequelae, drug-drug and drug-disease interactions. For these reasons, in the elderly, cyclobenzaprine should be used only if clearly needed. In such patients cyclobenzaprine should be initiated with a 5 mg dose and titrated slowly upward.

ADVERSE REACTIONS

ADVERSE REACTIONS Incidence of most common adverse reactions in the 2 double-blind, placebo-controlled 5 mg studies (incidence of greater than 3% on cyclobenzaprine hydrochloride 5 mg):

 | Cyclobenzaprine HCl 5 mg N=464 | Cyclobenzaprine HCl 10 mg N=249 | Placebo N=469
Drowsiness | 29% | 38% | 10%
Dry Mouth | 21% | 32% | 7%
Fatigue | 6% | 6% | 3%
Headache | 5% | 5% | 8%

Adverse reactions which were reported in 1% to 3% of the patients were: abdominal pain, acid regurgitation, constipation, diarrhea, dizziness, nausea, irritability, mental acuity decreased, nervousness, upper respiratory infection, and pharyngitis.

The following list of adverse reactions is based on the experience in 473 patients treated with cyclobenzaprine hydrochloride tablets 10 mg in additional controlled clinical studies, 7607 patients in the post-marketing surveillance program, and reports received since the drug was marketed. The overall incidence of adverse reactions among patients in the surveillance program was less than the incidence in the controlled clinical studies.

The adverse reactions reported most frequently with cyclobenzaprine hydrochloride were drowsiness, dry mouth and dizziness. The incidence of these common adverse reactions was lower in the surveillance program than in the controlled clinical studies:

Note: Cyclobenzaprine hydrochloride tablets 10 mg data are from one clinical trial. Cyclobenzaprine hydrochloride tablets 5 mg and placebo data are from two studies.

 | Clinical Studies With Cyclobenzaprine HCl 10 mg | Surveillance Progam With Cyclobenzaprine HCl 10 mg
Drowsiness | 39% | 16%
Dry Mouth | 27% | 7%
Dizziness | 11% | 3%

Among the less frequent adverse reactions, there was no appreciable difference in incidence in controlled clinical studies or in the surveillance program. Adverse reactions which were reported in 1% to 3% of the patients were: fatigue/tiredness, asthenia, nausea, constipation, dyspepsia, unpleasant taste, blurred vision, headache, nervousness, and confusion.

The following adverse reactions have been reported in post-marketing experience or with an incidence of less than 1% of patients in clinical trials with the 10 mg tablet:

Body as a Whole: Syncope; malaise.
Cardiovascular: Tachycardia; arrhythmia; vasodilatation; palpitation; hypotension.
Digestive: Vomiting; anorexia; diarrhea; gastrointestinal pain; gastritis; thirst; flatulence; edema of the tongue; abnormal liver function and rare reports of hepatitis, jaundice and cholestasis.
Hypersensitivity: Anaphylaxis; angioedema; pruritus; facial edema; urticaria; rash.
Musculoskeletal: Local weakness.
Nervous System and Psychiatric: Seizures, ataxia; vertigo; dysarthria; tremors; hypertonia; convulsions; muscle twitching; disorientation; insomnia; depressed mood; abnormal sensations; anxiety; agitation; psychosis, abnormal thinking and dreaming; hallucinations; excitement; paresthesia; diplopia.
Skin: Sweating.
Special Senses: Ageusia; tinnitus.
Urogenital: Urinary frequency and/or retention.

Causal Relationship Unknown

Other reactions, reported rarely for cyclobenzaprine hydrochloride under circumstances where a causal relationship could not be established or reported for other tricyclic drugs, are listed to serve as alerting information to physicians:

Body as a Whole: Chest pain; edema.
Cardiovascular: Hypertension; myocardial infarction; heart block; stroke.
Digestive: Paralytic ileus; tongue discoloration; stomatitis; parotid swelling.
Endocrine: Inappropriate ADH syndrome.
Hematic and Lymphatic: Purpura; bone marrow depression; leukopenia; eosinophilia; thrombocytopenia.
Metabolic, Nutritional and Immune: Elevation and lowering of blood sugar levels; weight gain or loss.
Musculoskeletal: Myalgia.
Nervous System and Psychiatric: Decreased or increased libido; abnormal gait; delusions; aggressive behavior; paranoia; peripheral neuropathy; Bell's palsy; alteration in EEG patterns; extrapyramidal symptoms.
Respiratory: Dyspnea.
Skin: Photosensitization; alopecia.
Urogenital: Impaired urination; dilatation of urinary tract; impotence; testicular swelling; gynecomastia; breast enlargement; galactorrhea.

DRUG ABUSE AND DEPENDENCE

Pharmacologic similarities among the tricyclic drugs require that certain withdrawal symptoms be considered when cyclobenzaprine hydrochloride is administered, even though they have not been reported to occur with this drug. Abrupt cessation of treatment after prolonged administration rarely may produce nausea, headache, and malaise. These are not indicative of addiction.

OVERDOSAGE
Although rare, deaths may occur from overdosage with cyclobenzaprine hydrochloride. Multiple drug ingestion (including alcohol) is common in deliberate cyclobenzaprine overdose. As management of overdose is complex and changing, it is recommended that the physician contact a poison control center for current information on treatment. Signs and symptoms of toxicity may develop rapidly after cyclobenzaprine overdose; therefore, hospital monitoring is required as soon as possible. The acute oral LD 50 of cyclobenzaprine hydrochloride is approximately 338 and 425 mg/kg in mice and rats, respectively.
MANIFESTATIONS
The most common effects associated with cyclobenzaprine overdose are drowsiness and tachycardia. Less frequent manifestations include tremor, agitation, coma, ataxia, hypertension, slurred speech, confusion, dizziness, nausea, vomiting, and hallucinations. Rare but potentially critical manifestations of overdose are cardiac arrest, chest pain, cardiac dysrhythmias, severe hypotension, seizures, and neuroleptic malignant syndrome. Changes in the electrocardiogram, particularly in QRS axis or width, are clinically significant indicators of cyclobenzaprine toxicity.
Other potential effects of overdosage include any of the symptoms listed under ADVERSE REACTIONS.
MANAGEMENT
General
As management of overdose is complex and changing, it is recommended that the physician contact a poison control center for current information on treatment.
In order to protect against the rare but potentially critical manifestations described above, obtain an ECG and immediately initiate cardiac monitoring. Protect the patient's airway, establish an intravenous line and initiate gastric decontamination. Observation with cardiac monitoring and observation for signs of CNS or respiratory depression, hypotension, cardiac dysrhythmias and/or conduction blocks, and seizures is necessary. If signs of toxicity occur at any time during this period, extended monitoring is required. Monitoring of plasma drug levels should not guide management of the patient. Dialysis is probably of no value because of low plasma concentrations of the drug.
Gastrointestinal Decontamination
All patients suspected of an overdose with cyclobenzaprine hydrochloride should receive gastrointestinal decontamination. This should include large volume gastric lavage followed by activated charcoal. If consciousness is impaired, the airway should be secured prior to lavage and emesis is contraindicated.
Cardiovascular
A maximal limb-lead QRS duration of less than equal than 0.10 seconds may be the best indication of the severity of the overdose. Serum alkalinization, to a pH of 7.45 to 7.55, using intravenous sodium bicarbonate and hyperventilation (as needed), should be instituted for patients with dysrhythmias and/or QRS widening. A pH >7.60 or a pCO2 less than 20 mmHg is undesirable. Dysrhythmias unresponsive to sodium bicarbonate therapy/hyperventilation may respond to lidocaine, bretylium or phenytoin. Type 1A and 1C antiarrhythmics are generally contraindicated (e.g., quinidine, disopyramide, and procainamide).
CNS
In patients with CNS depression, early intubation is advised because of the potential for abrupt deterioration. Seizures should be controlled with benzodiazepines or, if these are ineffective, other anticonvulsants (e.g., phenobarbital, phenytoin). Physostigmine is not recommended except to treat life-threatening symptoms that have been unresponsive to other therapies, and then only in close consultation with a poison control center.
PSYCHIATRIC FOLLOW-UP
Since overdosage is often deliberate, patients may attempt suicide by other means during the recovery phase. Psychiatric referral may be appropriate.
PEDIATRIC MANAGEMENT
The principles of management of child and adult overdosages are similar. It is strongly recommended that the physician contact the local poison control center for specific pediatric treatment.

DOSAGE AND ADMINISTRATION

For most patients, the recommended dose of cyclobenzaprine hydrochloride tablets is 5 mg three times a day. Based on individual patient response, the dose may be increased to 10 mg three times a day. Use of cyclobenzaprine hydrochloride tablets for periods longer than two or three weeks is not recommended (see INDICATIONS AND USAGE).

Less frequent dosing should be considered for hepatically impaired or elderly patients (see PRECAUTIONS, Impaired Hepatic Function, and Use in the Elderly).

HOW SUPPLIED
Cyclobenzaprine Hydrochloride Tablets, USP 5 mg round, orange film-coated tablets, debossed "2631" on one side and debossed "V" on the reverse side, supplied in bottles of 10, 100, 500 and 1000.
Cyclobenzaprine Hydrochloride Tablets, USP 10 mg round, yellow film-coated tablets, debossed "2632" on one side and debossed "V" on the reverse side, supplied in bottles of 10, 90, 100, 180, 270, 500, 1000 and 5000.
Manufactured for:
QUALITEST PHARMACEUTICALS
Huntsville, AL 35811
8181950
R6/11-R2

STORAGE AND HANDLING

Store at 20°-25°C (68°-77°F) [see USP Controlled Room Temperature].

KEEP OUT OF REACH OF CHILDREN

KEEP THIS AND ALL MEDICATION OUT OF THE REACH OF CHILDREN.

Theramine (U.S. patent pending) capsules by oral administration. A specially formulated Medical Food product, consisting of a proprietary blend of amino acids and polyphenol ingredients in specific proportions, for the dietary management of the metabolic processes associated with pain disorders and inflammatory conditions. (PD) (IC). Must be administered under physician supervision.
Medical Foods
Medical Food products are often used in hospitals (e.g., for burn victims or kidney dialysis patients) and outside of a hospital setting under a physician’s care for the dietary management of diseases in patients with particular, unique or distinctive medical or metabolic needs due to their disease or condition. Congress defined "Medical Food" in the Orphan Drug Act and Amendments of 1988 as "a food which is formulated to be consumed or administered enterally [or orally] under the supervision of a physician and which is intended for the specific dietary management of a disease or condition for which distinctive nutritional requirements, based on recognized scientific principles, are established by medical evaluation." Medical Foods are complex formulated products, requiring sophisticated and exacting technology, and that are used only for a patient receiving active and ongoing medical supervision wherein the patient requires medical care on a recurring basis for, among other things, instructions on the use of the Medical Food. Theramine has been developed, manufactured, and labeled in accordance with both the statutory definition of a Medical Food and FDA’s regulatory labeling guidelines. Theramine must be used while the patient is under the ongoing care of a physician.
PAIN DISORDERS (PD) INFLAMMATORY CONDITIONS (IC)
PD and IC as a Metabolic Deficiency Disease
A critical component of the definition of a Medical Food is that the product must address the distinct nutritional requirements of a particular disease or condition. FDA scientists have proposed a physiologic definition of distinctive nutritional requirements as follows: “the dietary management of patients with specific diseases requires, in some instances, the ability to meet nutritional requirements that differ substantially from the needs of healthy persons. For example, in establishing the recommended dietary allowances for general, healthy population, the Food and Nutrition Board of the Institute of Medicine National Academy of Sciences, recognized that different or distinctive physiologic requirements may exist for certain persons with "special nutritional needs arising from metabolic disorders, chronic diseases, injuries, premature birth, other medical conditions and drug therapies. Thus, the distinctive nutritional needs associated with a disease reflects the total amount needed by a healthy person to support life or maintain homeostasis, adjusted for the distinctive changes in the nutritional needs of the patient as a result of the effects of the disease process on absorption, metabolism and excretion.” It was also proposed that in patients with certain disease states who respond to nutritional therapies, a physiologic deficiency of the nutrient is assumed to exist. For example, if a patient with a pain disorder responds to a tryptophan formulation by decreasing perceived pain, then a deficiency of tryptophan is assumed to exist. Patients with pain disorders and inflammatory conditions are known to have increased nutritional requirements for tryptophan, choline, arginine, GABA, flavonoids, and certain antioxidants. These nutritional requirements are such that they cannot be achieved by the modification of the normal diet alone, or by supplementing the diet.
Patients with pain disorders and inflammatory conditions frequently exhibit reduced plasma levels of tryptophan and GABA, and have been shown to respond to oral administration of GABA, arginine, tryptophan, or a 5-hydroxytryptophan formulation. Research has shown that tryptophan, arginine or GABA reduced diets result in a fall of circulating tryptophan, arginine, and/or GABA. Patients with pain disorders frequently exhibit activation of the degradation pathways that increases the turnover rate of GABA, arginine and/or tryptophan leading to a reduced level of production of serotonin, GABA or nitric oxide for a given precursor blood level. Research has also shown that a genetic predisposition to accelerated degradation can lead to increased precursor requirements in certain patients with pain disorders and inflammatory conditions.
Choline is required to fully potentiate acetylcholine synthesis by brain neurons. A deficiency of choline leads to reduced acetylcholine production by the neurons. Provision of tryptophan, arginine, GABA, choline and flavonoids with antioxidants, in specific proportions can restore the production of beneficial serotonin, nitric oxide, and acetylcholine, thereby reducing the perception of pain and reducing inflammation. L-Histidine is known to produce brain histamine that stimulates production of ACTH, producing cortisol to reduce inflammation.

PRODUCT DESCRIPTION
Primary Ingredients
Theramine consists of a proprietary formulation of Gamma Aminobutyric Acid, Choline Bitartrate, Whey Protein Hydrolysate, L-Arginine, L-Histidine, L-Glutamine, Theobromine, Griffonia See, Grape Seed, L-Serine, and Cinnamon in specific proportions. These ingredients fall into the classification of Generally Recognized as Safe (GRAS) as defined by the Food and Drug Administration (FDA) (Sections 201(s) and 409 of the Federal Food, Drug, and Cosmetic Act). A GRAS substance is distinguished from a food additive on the basis of the common knowledge about the safety of the substance for its intended use. The standard for an ingredient to achieve GRAS status requires not only technical demonstration of non-toxicity and safety, but also general recognition of safety through widespread usage and agreement of that safety by experts in the field. Many ingredients have been determined by the FDA to be GRAS, and are listed as such by regulation, in Volume 21 Code of Federal Regulations (CFR) Sections 182, 184, and 186.
Amino Acids
Amino Acids are the building blocks of protein and are GRAS listed as they have been safely ingested by humans for thousands of years. The formulations of the amino acids in Theramine are equivalent to those found in the usual human diet. Patients with pain disorders may require an increased amount of certain amino acids that cannot be obtained from normal diet alone. Tryptophan, for example, is an obligatory amino acid. The body cannot make tryptophan and must obtain tryptophan from the diet. Tryptophan is needed to produce serotonin. Serotonin is required to reduce pain. Patients with pain disorders and inflammatory conditions have altered serotonin metabolism.
Flavonoids
Flavonoids are a group of phytochemical compounds found in all vascular plants including fruits and vegetables. They are a part of a larger class of compounds known as polyphenols. Many of the therapeutic or health benefits of colored fruits and vegetables, cocoa, red wine, and green tea are directly related to their flavonoid content. The specially formulated flavonoids found in Theramine cannot be obtained from conventional foods in the necessary proportions to elicit a therapeutic response.
Other Ingredients
Theramine contains the following “inactive” or other ingredients, as fillers, excipients, and colorings: Gelatin, Silicon Dioxide, Tricalcium Phosphate, Vegetable Magnesium stearate, Cellulose, FDandC Blue#1, FDandC Red #3, Titanium Dioxide.
Physical Description
Theramine is a yellow to light brown powder. Theramine contains Gamma Aminobutyric Acid, Choline Bitartrate, Whey Protein Hydrolysate, L-Arginine, L-Histidine HCL, L-Glutamine, Theobromine, Griffonia Seed, Grape Seed, L-Serine, and Cinnamon. Each capsule consists of a proprietary blend of these ingredients in an amount of 366mg or 732mg per two (2) capsule dose.

CCLINICAL PHARMACOLOGY
Mechanism of Action
Theramine acts by restoring and maintaining the balance of the neurotransmitters GABA, nitric oxide, serotonin, and acetylcholine that are associated with pain disorders and inflammatory conditions. Theramine stimulates the production ACTH to reduce inflammation.
Metabolism
The amino acids in Theramine are primarily absorbed by the stomach and small intestines. All cells metabolize the amino acids in Theramine. Circulating tryptophan, arginine and choline blood levels determine the production of serotonin, nitric oxide, and acetylcholine.
Excretion
Theramine is not an inhibitor of cytochrome P450 1A2, 2C9, 2C19, 2D6, or 3A4. These isoenzymes are principally responsible for 95% of all detoxification of drugs, with CYP3A4 being responsible for detoxification of roughly 50% of drugs. Amino acids do not appear to have an effect on drug metabolizing enzymes.

INDICATIONS FOR USE
Theramine is intended for the clinical dietary management of the metabolic processes of pain disorders and inflammatory conditions.

CLINICAL EXPERIENCE
Administration of Theramine has demonstrated significant reduction in symptoms of pain and inflammation in patients with acute and chronic pain when used
for the dietary management of the metabolic processes associated with pain disorders and inflammatory conditions. Administration of Theramine results in
the induction and maintenance of pain relief in patients with pain disorders and inflammatory conditions.

PRECAUTIONS AND CONTRAINDICATIONS
Theramine is contraindicated in an extremely small number of patients with hypersensitivity to any of the nutritional components of Theramine.

ADVERSE REACTIONS
Ingestion of L-Tryptophan, L-Arginine, or Choline at high doses of up to 15 grams daily is generally well tolerated. The most common adverse reactions of higher
doses — from 15 to 30 grams daily — are nausea, abdominal cramps, and diarrhea. Theramine contains less than 1 gram per dose of amino acids however, some patients
may experience these symptoms at lower doses. The total combined amount of amino acids in each Theramine capsule does not exceed 300 mg.

DRUG INTERACTIONS
Theramine does not directly influence the pharmacokinetics of prescription drugs. Clinical experience has shown that administration of Theramine may allow for lowering the dose of co-administered drugs under physician supervision.

OVERDOSAGE

OVERDOSE
There is a negligible risk of overdose with Theramine as the total amount of amino acids in a one month supply (90 capsules) is less than 30 grams. Overdose symptoms may include diarrhea, weakness, and nausea.
POST-MARKETING SURVEILLANCE
Post-marketing surveillance has shown no serious adverse reactions. Reported cases of mild rash and itching may have been associated with allergies to Theramine flavonoid ingredients, including Cinnamon, Cocoa, and Grape Seed. These reactions were temporary, transient in nature and subsided within 24-hours.

DOSAGE AND ADMINISTRATION
Recommended Administration
For the dietary management of the metabolic processes associated with pain disorders and inflammatory conditions. Take two (2) capsules every four hours or as directed by physician. As with most amino acid formulations Theramine should be taken without food to increase the absorption of key ingredients.

How Supplied
Theramine is supplied in purple and white, size 0 capsules in bottles of 60 and 90 capsules.
Physician Supervision
Theramine is a Medical Food product available by prescription only and may be used per FDA law, and product labeling only while the patient is under ongoing physician supervision.
U.S. patent pending
Manufactured by Arizona Nutritional Supplements, Inc. Chandler AZ 85225
Distributed exclusively by Physician Therapeutics LLC, a wholly owned subsidiary of Targeted Medical Pharma Inc. Los Angeles, CA
www.ptlcentral.com NDC: 68405-008-02 NDC: 68405-008-03

Storage
Store in a cool dry place 45-90ο F (8-32ο C) relative humidity below 50%. Theramine is supplied in a recyclable plastic bottle with a child-resistant cap.

PACKAGE LABEL

68405-008-02 Directions for use: Must be administered under physician supervision. For adults only. As a Medical Food, take one (1) or two (2) capsules every four hours or as directed by physician. For the dietary management of Myalgia. Contains no added sugar, starch, wheat, yeast, preservatives, artificial flavor. Storage: Keep tightly closed in a cool dry place 8-32°C (45-90°F), relative humidity, below 50%. Warning: Keep this product out of the reach of children. NDC# 68405-008-02 LOT# 007007 PHYSICIAN THERAPEUTICS THERAMINE Medical Food Rx only 60 Capsules Ingredients: Each serving (per 2 capsules) contains: Proprietary Amino Acid Formulation Whey Protein Hydrolysate (milk sourced isolate), L-Arginine (as L-Arginine HCl), L-Histidine HCI, L-Glutamine, L-Serine Gamma Amino Butyric Acid Choline Bitartrate Griffonia Seed Extract (5-HTP) Cocoa Extract (6% Theobromine) Grape Seed Extract (85% Polyphenols) Cinnamon (bark) Other Ingredients: Gelatin, Tricalcium Phosphate, Silicon Dioxide, Magnesium Stearate, Microcrystalline Cellulose, Titanium Dioxide, FDandC Red #3, FDandC Blue #1. Distributed exclusively by: Physicians Therapeutics A Division of Targeted Medical Pharma, Inc. Los Angeles, CA 90077 www.ptlcentral.com US Patent 7,582,315; 7,585,523; 7,595,067; 7,601,369. LOT 007007 EXP 08/13

PACKAGE LABEL

A Convenience Packed Medical Food and Drug Therabenzaprine-60 PHYSICIAN THERAPEUTICS > Theramine 60 Capsules > Cyclobenzaprine 10 mg 60 Tablets No Refills Without Physician Authorization Rx Only NDC# 68405-580-26 of this co-pack